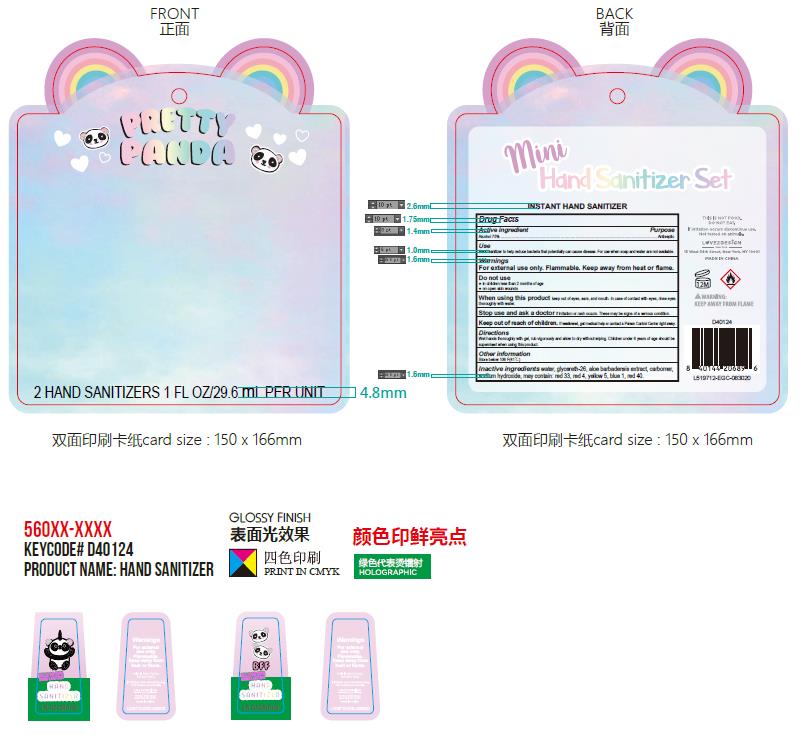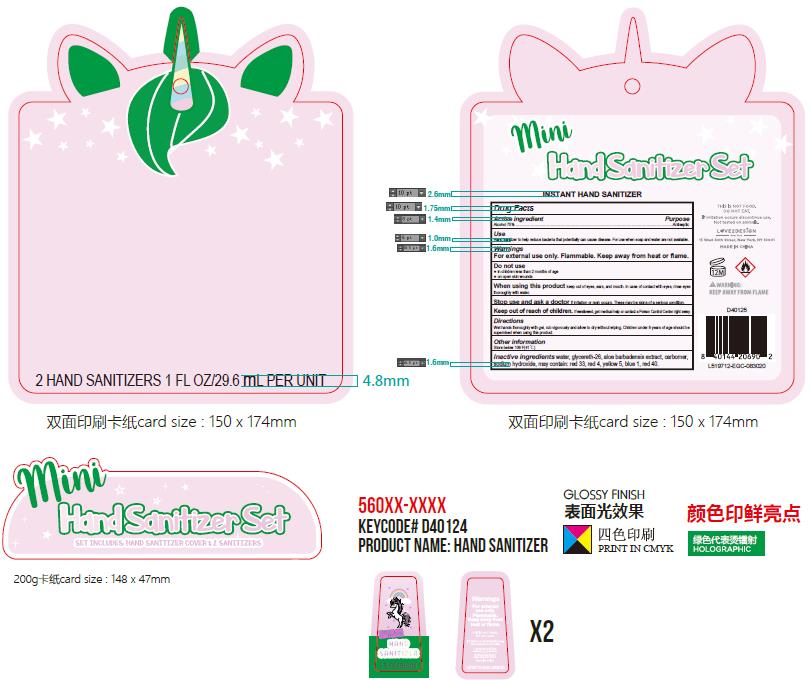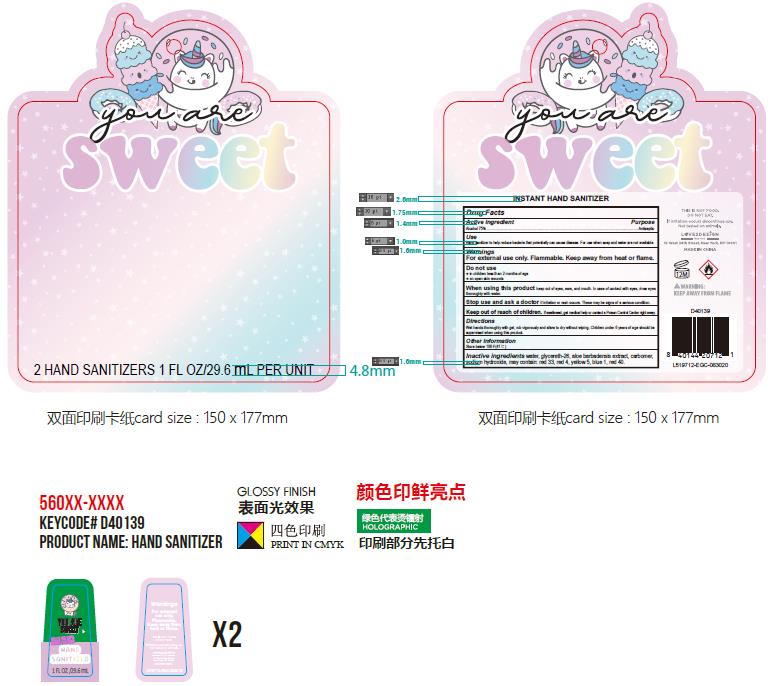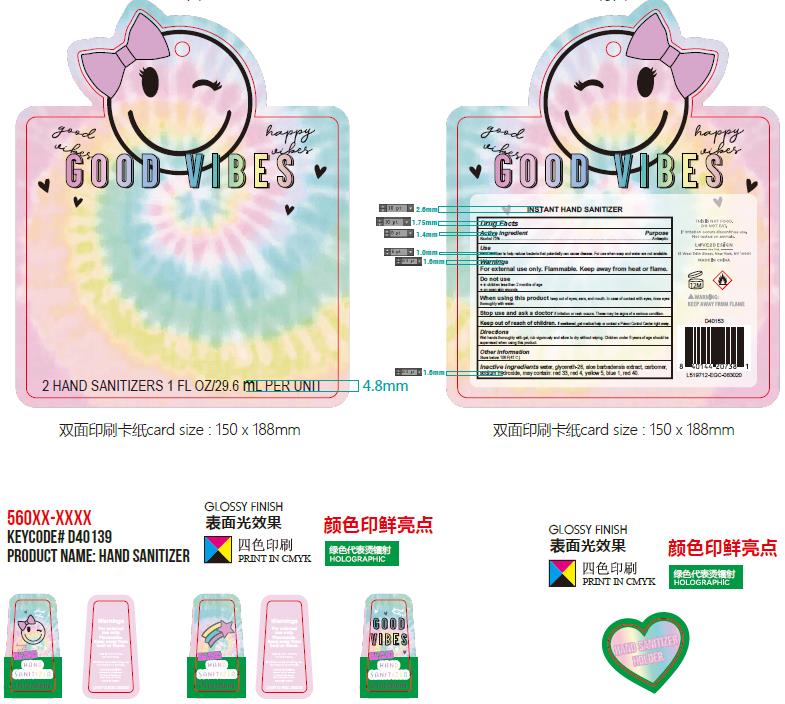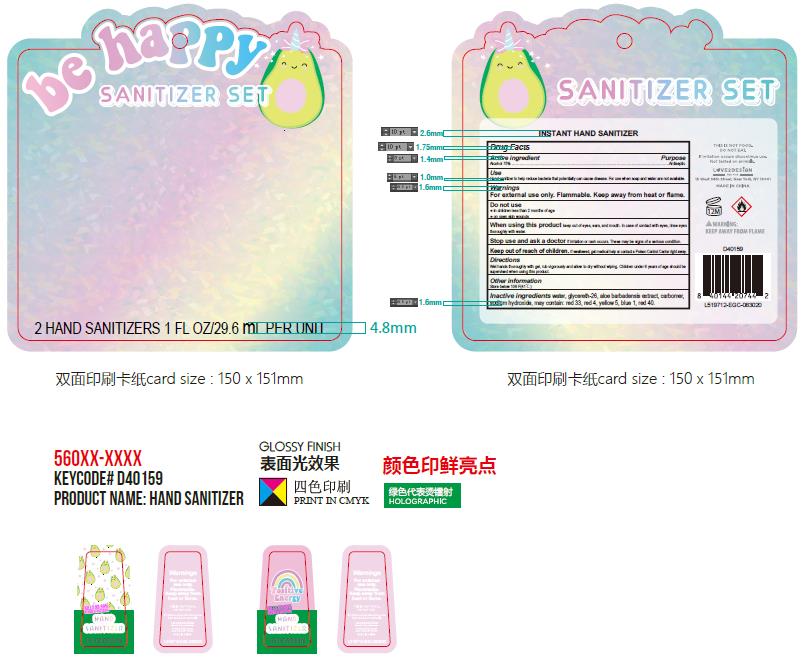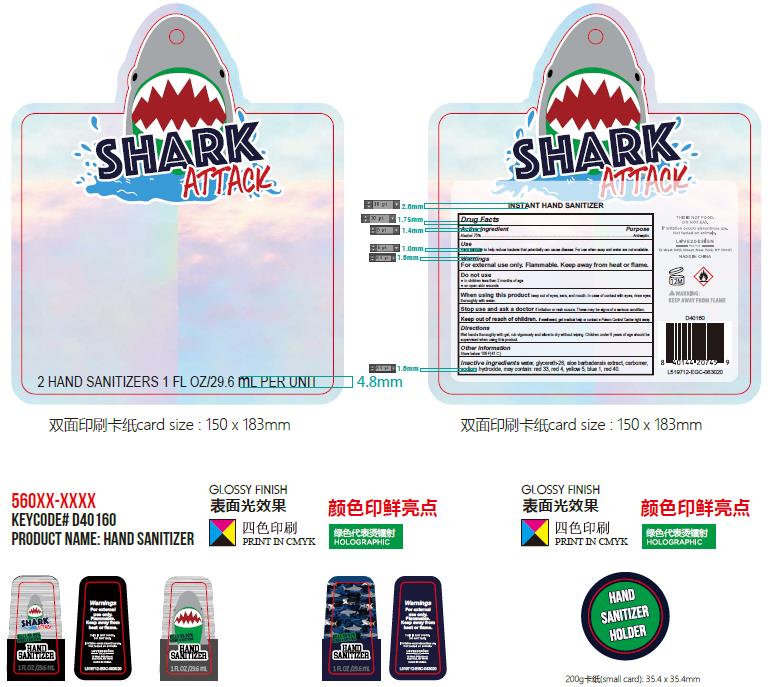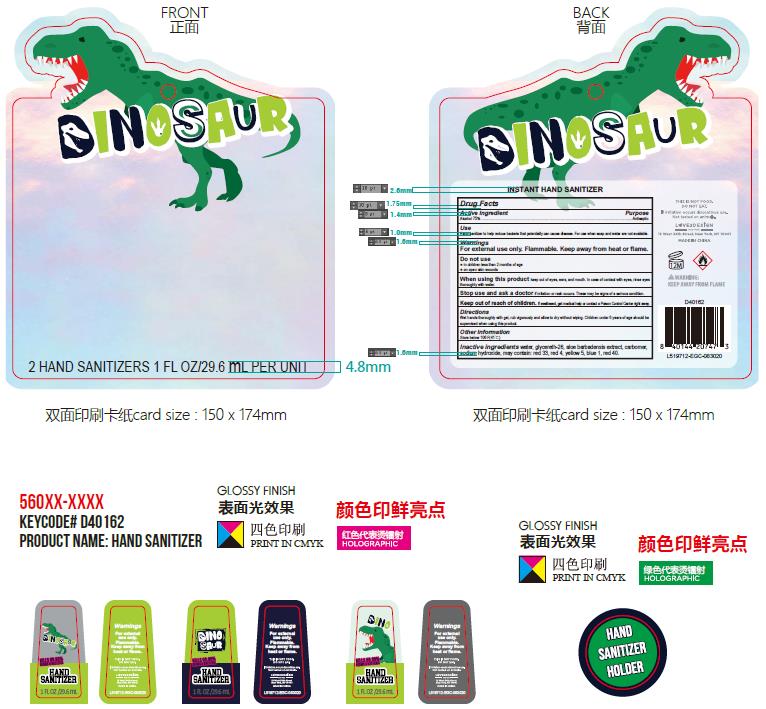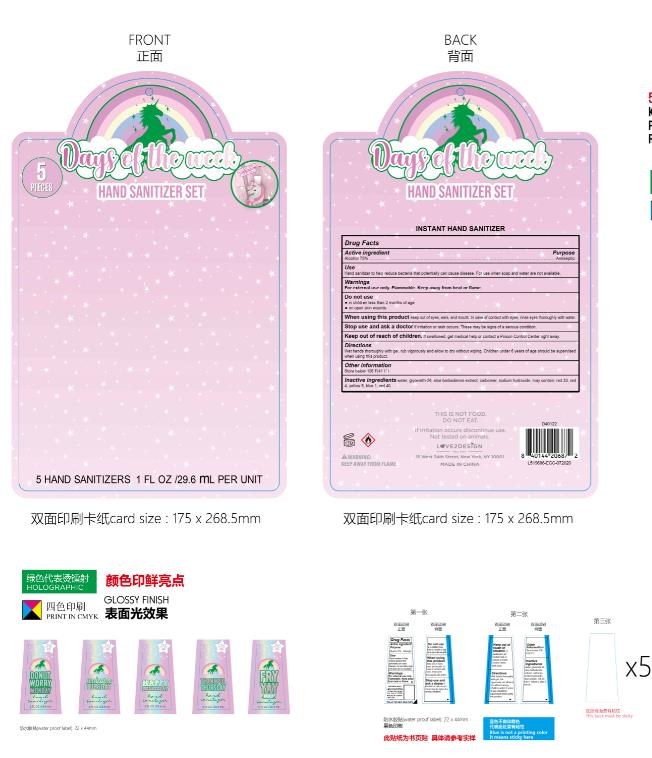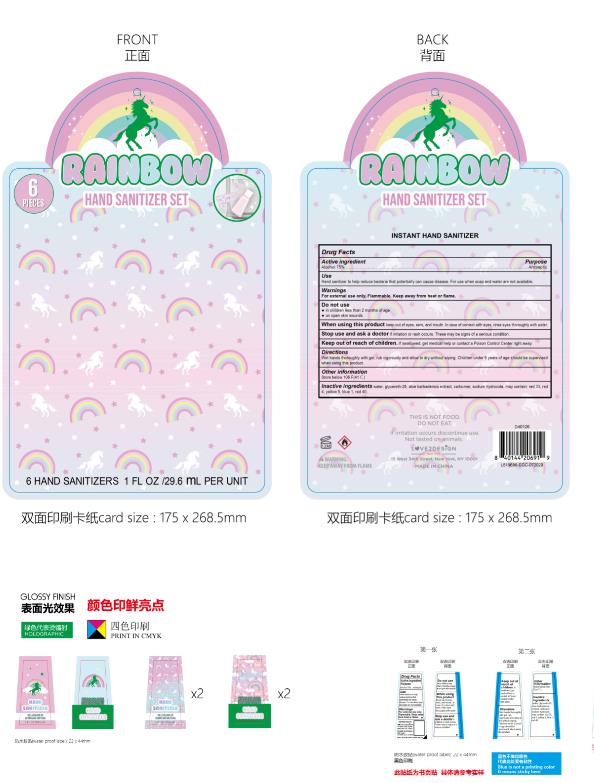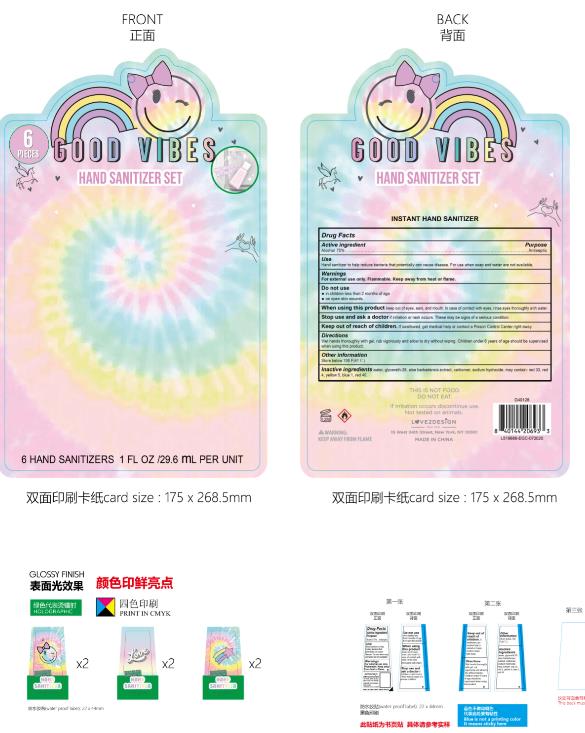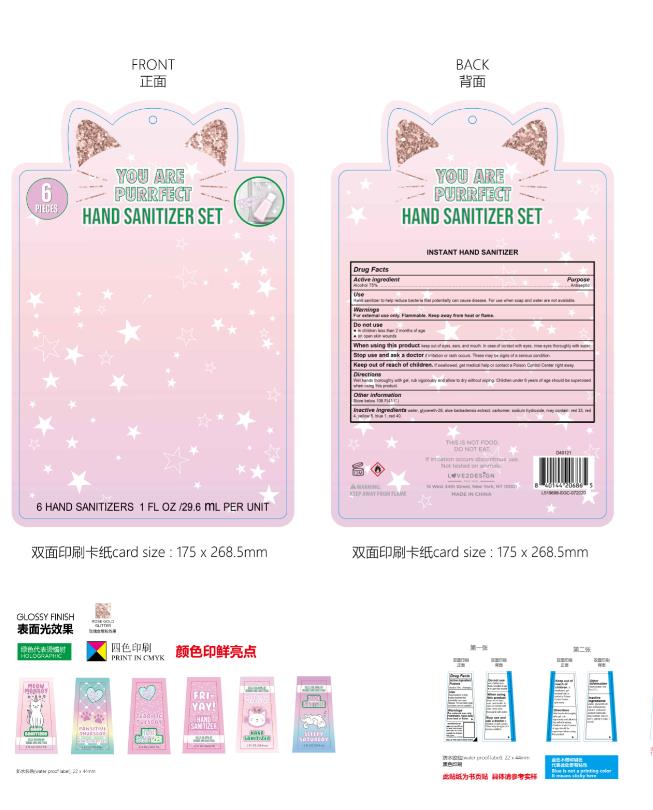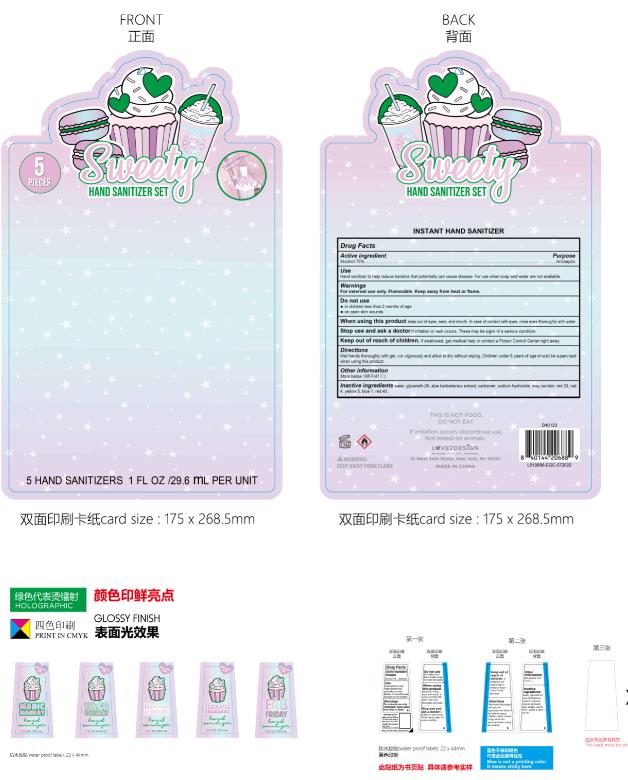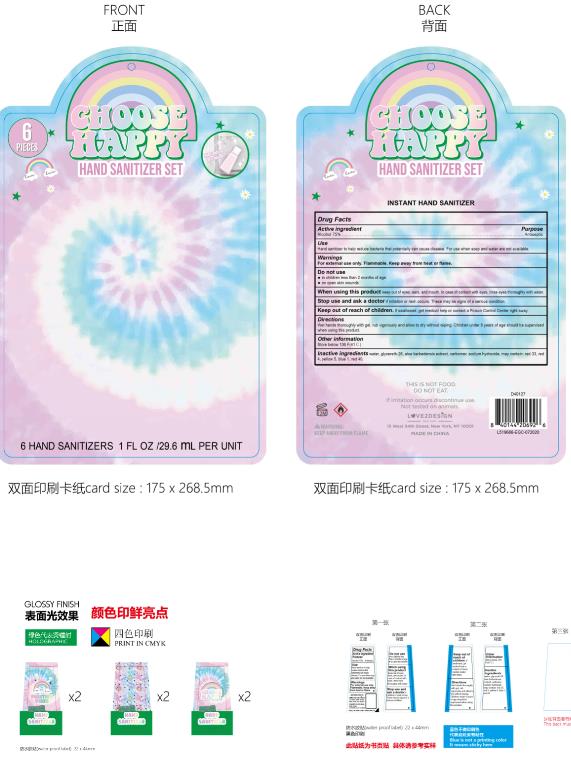 DRUG LABEL: HAND SANITIZER SET
NDC: 74657-004 | Form: GEL
Manufacturer: Double Body Biotech Limited
Category: otc | Type: HUMAN OTC DRUG LABEL
Date: 20200804

ACTIVE INGREDIENTS: ALCOHOL 75 mL/100 mL
INACTIVE INGREDIENTS: FD&C YELLOW NO. 5; SODIUM HYDROXIDE; FD&C RED NO. 4; GLYCERETH-26; CARBOXYPOLYMETHYLENE; FD&C BLUE NO. 1; FD&C RED NO. 40; WATER; ALOE; D&C RED NO. 33

Active ingredient

Alcohol 75%

Purpose

Antiseptic

Use

Hand sanitizer to help reduce bacteria that potentially can cause disease. For use when soap and water are not available.

Warnings

For external use only. Flammable. Keep away heat or flame.

Do not use

- in children less than 2 months of age
- on open skin wounds

When using this product keep out of eyes, ears, and mouth. In case of contact with eyes, rinse eyes thoroughly with water.

Keep out of reach of children

If swallowed, get medical help or contact a Poison Control Center right away.

Stop use and ask a doctor if irritation or rash occurs. These may be signs of a serious condition.

Directions

Wet hands thoroughly with gel, rub vigorously and allow to dry without wiping. Children under 6 years of age should be supervised when using this product.

Other information

Store below 106 F(41 C)

Inactive ingredients

water

glycereth-26

aloe barbadensis extract,

carbomer,

sodium hydroxide,

may contain: red 33, red 4, yellow 5, blue 1, red 40.